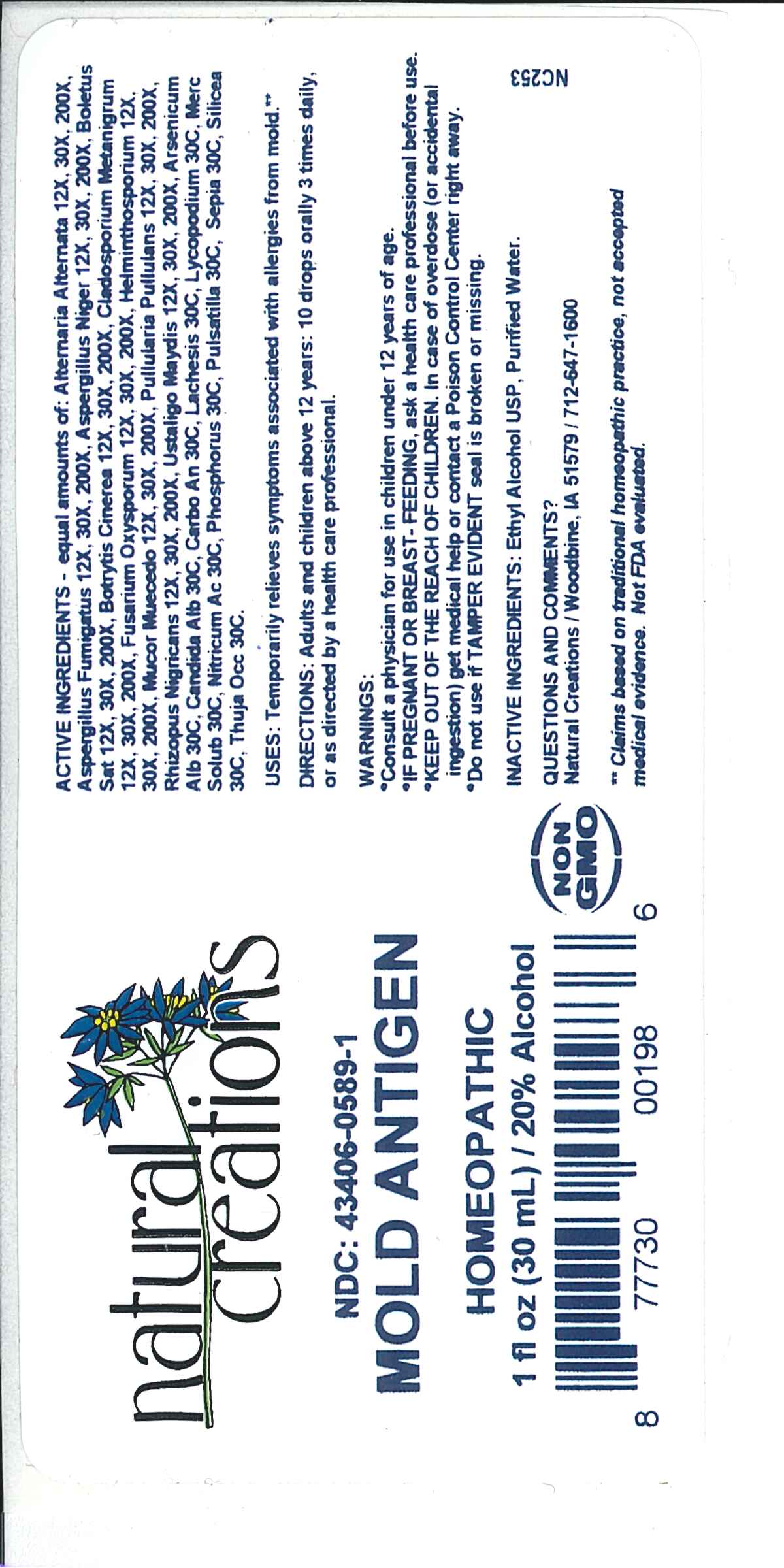 DRUG LABEL: Mold Antigen
NDC: 43406-0589 | Form: LIQUID
Manufacturer: Natural Creations, Inc
Category: homeopathic | Type: HUMAN OTC DRUG LABEL
Date: 20251216

ACTIVE INGREDIENTS: ALTERNARIA ALTERNATA 200 [hp_X]/1 mL; ASPERGILLUS FUMIGATUS 200 [hp_X]/1 mL; ASPERGILLUS NIGER VAR. NIGER 200 [hp_X]/1 mL; BOLETUS SATANAS FRUITING BODY 200 [hp_X]/1 mL; BOTRYTIS CINEREA 200 [hp_X]/1 mL; AUREOBASIDIUM PULLULANS VAR. PULLUTANS 200 [hp_X]/1 mL; FUSARIUM OXYSPORUM 200 [hp_X]/1 mL; COCHLIOBOLUS SATIVUS 200 [hp_X]/1 mL; RHIZOPUS STOLONIFER 200 [hp_X]/1 mL; USTILAGO MAYDIS 200 [hp_X]/1 mL; ARSENIC TRIOXIDE 30 [hp_C]/1 mL; CANDIDA ALBICANS 30 [hp_C]/1 mL; CARBO ANIMALIS 30 [hp_C]/1 mL; LACHESIS MUTA VENOM 30 [hp_C]/1 mL; LYCOPODIUM CLAVATUM SPORE 30 [hp_C]/1 mL; MERCURIUS SOLUBILIS 30 [hp_C]/1 mL; NITRIC ACID 30 [hp_C]/1 mL; PHOSPHORUS 30 [hp_C]/1 mL; PULSATILLA VULGARIS WHOLE 30 [hp_C]/1 mL; SEPIA OFFICINALIS JUICE 30 [hp_C]/1 mL; SILICON DIOXIDE 30 [hp_C]/1 mL; THUJA OCCIDENTALIS LEAFY TWIG 30 [hp_C]/1 mL
INACTIVE INGREDIENTS: ALCOHOL; WATER

Mold Antigen

ACTIVE INGREDIENT

ACTIVE INGREDIENTS - equal amounts of: Alternaria Alternata 12X, 30X, 200X, Aspergillus Fumigatus 12X, 30X, 200X, Aspergillus Niger 12X, 30X, 200X, Boletus Sat 12X, 30X, 200X, Botrytis Cinerea 12X, 30X, 200X, Cladosporium Metanigrum 12X, 30X, 200X, Fusarium Oxysporum 12X, 30X, 200X, Helminthosporium 12X, 30X, 200X, Mucor Muecedo 12X, 30X, 200X, Pullularia Pullulans 12X, 30X, 200X, Rhizopus Nigricans 12X, 30X, 200X, Ustilago Maydis 12X, 30X, 200X, Arsenicum Alb 30C, Candida Alb 30C, Carbo An 30C, Lachesis 30C, Lycopodium 30C, Merc Solub 30C, Nitricum Ac 30C, Phosphorus 30C, Pulsatilla 30C, Sepia 30C, Silicea 30C, Thuja Occ 30C

INDICATIONS AND USAGE

USES: Temporarily relieves symptoms associated with allergies from mold.**

PURPOSE

USES: Temporarily relieves symptoms associated with allergies from mold.**

DOSAGE AND ADMINISTRATION

DIRECTIONS: Adults & children above 12 years: 10 drops orally 3 times daily, or as directed by a health care professional.

KEEP OUT OF REACH OF CHILDREN

KEEP OUT OF THE REACH OF CHILDREN. In case of overdose (or accidental ingestion) get medical help or contact a Poison Control Center right away.

WARNINGS:

- Consult a physician for use in children under 12 years of age.
- IF PREGNANT OR BREAST-FEEDING, ask a health care professional before use.
- KEEP OUT OF THE REACH OF CHILDREN. In case of overdose (or accidental ingestion) get medical help or contact a Poison Control Center right away.
- Do not use if TAMPER EVIDENT seal is broken or missing.

INACTIVE INGREDIENTS: Ethyl Alcohol USP, Purified Water

QUESTIONS & COMMENTS?

Natural Creations, Inc. / Woodbine, IA 51579 / 712-647-1600

REFERENCES

**Claims based on traditional homeopathic practice, not accepted medical evidence. Not FDA evaluated.

PACKAGE LABEL

NDC:43406-0589-1

Mold Antigen

HOMEOPATHIC

1 fl oz (30mL) / 20% Alcohol